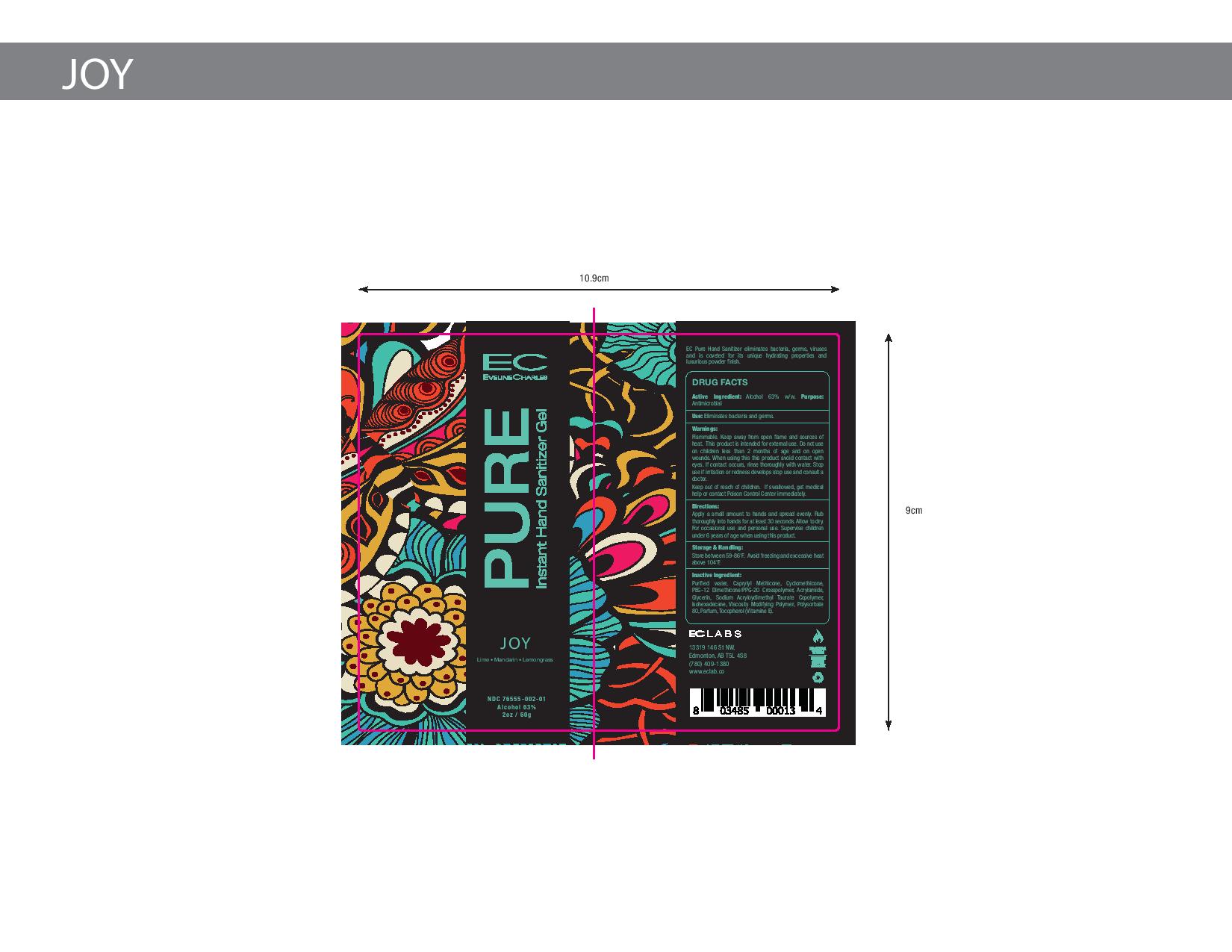 DRUG LABEL: EC Pure Instant Cream Hand Sanitizer Joy
NDC: 76555-002 | Form: CREAM
Manufacturer: Ec Labs Inc
Category: otc | Type: HUMAN OTC DRUG LABEL
Date: 20220114

ACTIVE INGREDIENTS: ALCOHOL 37.8 g/60 g
INACTIVE INGREDIENTS: WEST INDIAN LEMONGRASS OIL 0.00022 g/60 g; BERGAMOT OIL 0.00036 g/60 g; LIME OIL 0.00042 g/60 g; CITRUS RETICULATA LEAF OIL 0.0003 g/60 g; MANDARIN OIL 0.00034 g/60 g; CANANGA OIL 0.00016 g/60 g; LEMON OIL 0.00052 g/60 g; ORANGE OIL 0.00052 g/60 g; AMMONIUM ACRYLOYLDIMETHYLTAURATE, DIMETHYLACRYLAMIDE, LAURYL METHACRYLATE AND LAURETH-4 METHACRYLATE COPOLYMER, TRIMETHYLOLPROPANE TRIACRYLATE CROSSLINKED (45000 MPA.S) 0.78 g/60 g; GLYCERIN 0.3 g/60 g; TOCOPHEROL 0.06 g/60 g; CYCLOMETHICONE 1.02 g/60 g; PEG/PPG-18/12 DIMETHICONE 5.1 g/60 g; SODIUM ACRYLOYLDIMETHYLTAURATE 1.74 g/60 g; WATER 13.2 g/60 g

Eveline Charles Pure Instant Cream Hand Sanitizer Joy

Active Ingredient(s)

Alcohol 63% w/w. Purpose: Antimicrobial

Use

Eliminates bacteria and germs.

Warnings

Flammable. Keep away from open flame and sources of heat.

This product is intended for external use only.

Do not use on children less than 2 months of age and on open wounds.

When using this product avoid contact with eyes. If contact occurs, rinse thoroughly with water.

Stop use if irritation or redness develops stop use and consult a doctor.

KEEP OUT OF REACH OF CHILDREN

Keep out the reach of children. if swallowed, get medical help or contact Poison Control Center right away.

Directions

Apply a small amount to hands and spread evenly.

Rub thoroughly into hands for at least 30 seconds.

Allow to dry.

For occasional and personal use.

Supervise children under 6 years of age when using this product.

Other information

- Store between 59-86F
- Avoid freezing and excessive heat above 104F.

Inactive ingredients

Purified water, Caprylyl Methicone, Cyclomethicone, PEG-12 Dimethicone/PPG-20 Crosspolymer, Acrylamide, Glycerin, Sodium Acryloyldimethyl Taurate Copolymer, Isohexadecane, Viscosity Modifying Polymer, Polysorbate 80, Parfum, Tocopherol (Vitamin E).

PURPOSE

Antimicrobial, Hand Sanitizer

Package Label - Principal Display Panel

60g NDC 76555-002-01